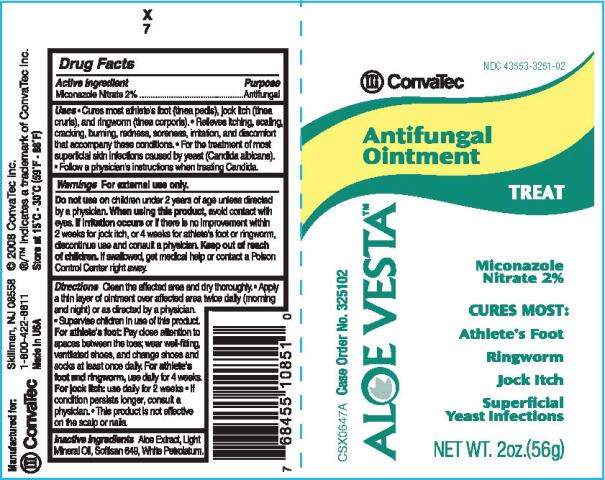 DRUG LABEL: ALOE VESTA ANTIFUNGAL
NDC: 43553-3251 | Form: OINTMENT
Manufacturer: ConvaTec, Inc.
Category: otc | Type: HUMAN OTC DRUG LABEL
Date: 20110408

ACTIVE INGREDIENTS: MICONAZOLE NITRATE 20 mg/1 g
INACTIVE INGREDIENTS: ALOE VERA LEAF; LIGHT MINERAL OIL; PETROLATUM

Drug Facts

Active Ingredient

Miconazole Nitrate 2%

Purpose

Antifungal

Uses

- Cures most athlete's foot (tinea pedis), jock itch (tinea cruris), and ringworm (tinea corporis).
- Relieves itching, scaling, cracking, burning, redness, soreness, irritation, and discomfort that accompany these conditions.
- For the treatment of most superficial skin infections caused by yeast (Candida albicans).
- Follow a physician's instructions when treating Candida.

Warnings

For external use only.

Do not use on

children under 2 years of age unless directed by a physician.

When using this product,

avoid contact with eyes.

If irritation occurs

or if there is no improvement within 2 weeks for jock itch, or 4 weeks for athlete's foot or ringworm, discontinue use and consult a physician.

Keep out of reach of children.

If swallowed, get medical help or consult a Poison Control Center right away.

Directions

Clean the affected area and dry thoroughly.

- Apply a thin layer of ointment over affected area twice daily (morning and night) or as directed by a physician.
- Supervise children in use of this product.

For athlete's foot: Pay close attention to spaces between the toes; wear well-fitting, ventilated shoes, and change shoes and socks at least once daily.
For athlete's foot and ringworm, use daily for 4 weeks.
For jock itch: use daily for 2 weeks

- If condition persists longer, consult a physician.
- This product is not effective on the scalp or nails.

Other Information

Store at 15oC - 30oC (59oF - 86oF).

Inactive Ingredients

Aloe Extract, Light Mineral Oil, Softisan 649, White Petrolatum.

PRINCIPAL DISPLAY PANEL

NDC 43553-3251-2

ConvaTec

ALOE VESTATM

Antifungal Ointment

TREAT

Miconazole Nitrate 2%

CURES MOST:

Athlete's Foot

Ringworm

Jock Itch

Superficial Yeast Infections

NET WT. 2oz.(56g)

CSX0647A Case Order No. 325102